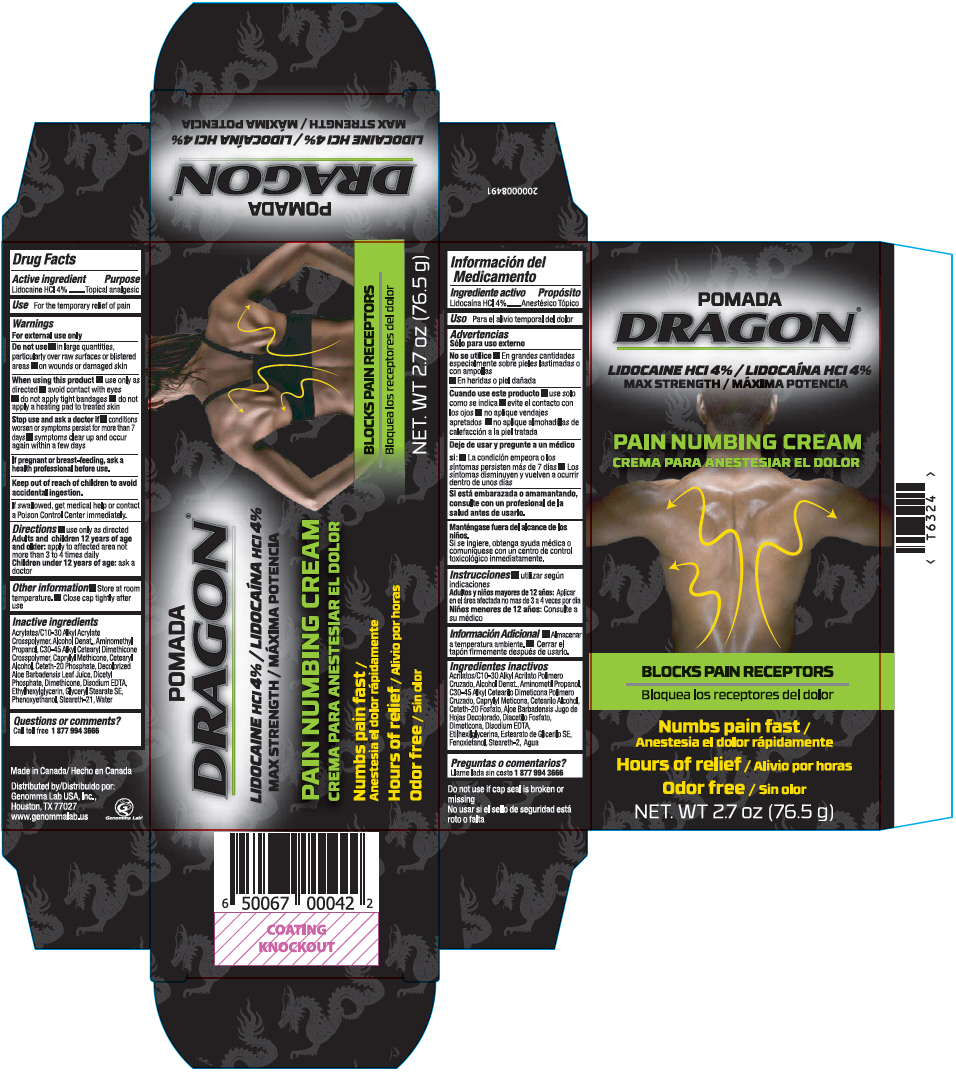 DRUG LABEL: Dragon Pain Numbing
NDC: 50066-056 | Form: CREAM
Manufacturer: Genomma Lab USA Inc.
Category: otc | Type: HUMAN OTC DRUG LABEL
Date: 20241113

ACTIVE INGREDIENTS: LIDOCAINE HYDROCHLORIDE 40 mg/1 g
INACTIVE INGREDIENTS: CARBOMER INTERPOLYMER TYPE A (ALLYL SUCROSE CROSSLINKED); ALCOHOL; AMINOMETHYLPROPANOL; CAPRYLYL TRISILOXANE; CETOSTEARYL ALCOHOL; Ceteth-20 Phosphate; ALOE VERA LEAF; DIHEXADECYL PHOSPHATE; Dimethicone; EDETATE DISODIUM; Ethylhexylglycerin; Glyceryl Stearate SE; Phenoxyethanol; Steareth-21; Water

Dragon® Pain Numbing Cream

Drug Facts

Active ingredient

Lidocaine HCl 4%

Purpose

Topical analgesic

Uses

for the temporary relief of pain

Warnings

For external use only

Do not use

- on large areas of the body or on raw or blistered skin
- on wounds or damaged skin

When using this product

- use only as directed
- do not use in large quantities
- avoid contact with eyes
- do not apply tight bandages
- do not apply a heating pad to treated skin

Stop use and ask a doctor if

- conditions worsen or symptoms persist for more than 7 days
- symptoms clear up and occur again within a few days

PREGNANCY OR BREAST FEEDING

If pregnant or breast-feeding, ask a health professional before use.

Keep out of reach of children to avoid accidental ingestion.

If swallowed, get medical help or contact a Poison Control Center immediately.

Directions

- use only as directed Adults and children 12 years of age and older: apply to affected area not more than 3 to 4 times daily Children under 12 years of age: ask a doctor

Other information

- Store at room temperature
- Close cap tightly after use

Inactive ingredients

Acrylates/C10-30 Alkyl Acrylate Crosspolymer, Alcohol denat., Aminomethyl propanol, C30-45 Alkyl Cetearyl Dimethicone Crosspolymer, Caprylyl Methicone, Cetearyl Alcohol, Ceteth-20 Phosphate, Decolorized Aloe barbadensis leaf juice, Dicetyl Phosphate, Dimethicone, Disodium EDTA, Ethylhexylglycerin, Glyceryl Stearare SE, Phenoxyethanol, Steareth-21, Water

Questions or comments?

Call toll free 1 877 99 GENOM (43666)

Distributed by:
Genomma Lab USA, Inc.,
Houston, TX 77027

PRINCIPAL DISPLAY PANEL - 76.5 g Bottle Carton

POMADA
DRAGON®

LIDOCAINE HCl 4%
MAX STRENGTH

PAIN NUMBING CREAM

BLOCKS PAIN RECEPTORS

Numbs pain fast

Hours of relief

Odor free

NET. WT 2.7 oz (76.5 g)